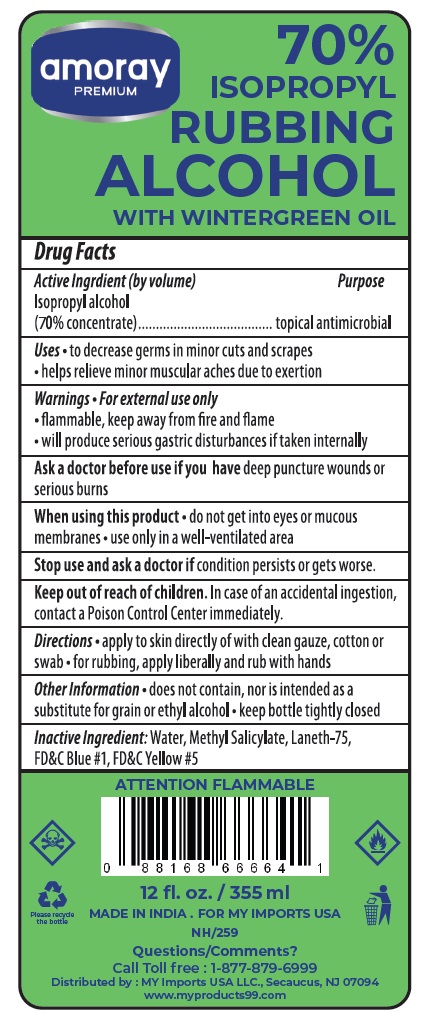 DRUG LABEL: 70% ISOPROPYL RUBBING ALCOHOL WITH WINTERGREEN
NDC: 30400-705 | Form: LIQUID
Manufacturer: Jell Pharmaceuticals Pvt. Ltd.
Category: otc | Type: HUMAN OTC DRUG LABEL
Date: 20250822

ACTIVE INGREDIENTS: ISOPROPYL ALCOHOL 70 mL/100 mL
INACTIVE INGREDIENTS: WATER; METHYL SALICYLATE; LANETH-75; FD&C BLUE NO. 1; FD&C YELLOW NO. 5

70% ISOPROPYL RUBBING ALCOHOL WITH WINTERGREEN

Active ingredient (by volume)

Isopropyl alcohol (70% concentrate)

Purpose

topical antimicrobial

Uses

- to decrease germs in minor cuts and scrapes
- helps relieve minor muscular aches due to exertion

Warnings

For external use only

- flammable, keep away from fire and flame
- will produce serious gastric disturbances if taken internally

Ask a doctor before use if you havedeep puncture wounds or serious burns

When using this product

- do not get into eyes or mucous membranes
- use only in a well-ventilated area

Stop use and ask a doctor ifcondition persists or gets worse

Keep out of reach of children.

In case of an accidental ingestion, contact a Poison Control Center immediately

Directions

- apply to skin directly of with clean gauze, cotton or swab
- for rubbing apply liberally and rub with hands

Other information

- does not contain, nor is intended as a substitute for grain or ethyl alcohol
- keep bottle tightly closed

Inactive ingredient

Water, Methyl Salicylate, Laneth-75, FD&C Blue #1, FD&C Yellow #5